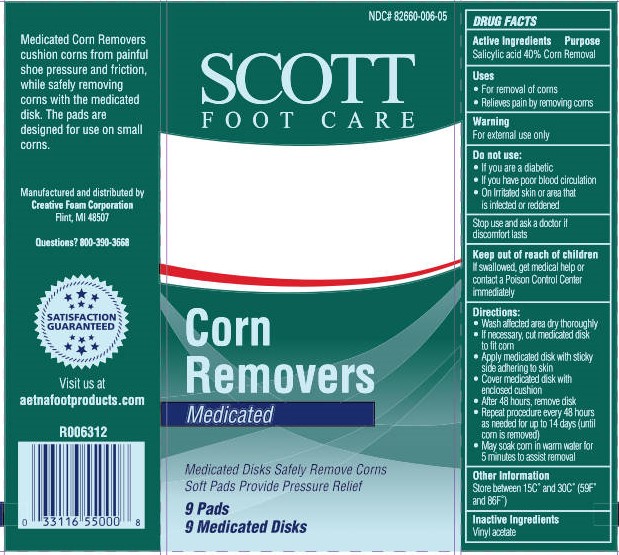 DRUG LABEL: Scott Clear Corn Removers
NDC: 82660-006 | Form: PLASTER
Manufacturer: Creative Foam Corporation
Category: otc | Type: HUMAN OTC DRUG LABEL
Date: 20251205

ACTIVE INGREDIENTS: SALICYLIC ACID 40 mg/100 mg
INACTIVE INGREDIENTS: POLYVINYL ALCOHOL, UNSPECIFIED; ACRYLIC ACID/ETHYLENE COPOLYMER (600 MPA.S)

Scott Foot Care Clear Corn Removers

Active Ingredient

Salicylic Acid 40% w/w

Purpose

Corn Removal

Uses

- For removal of corns
- Relieves pain by removing corns

Warning

For external use only

Do not use:

- If you are a diabetic
- If you have poor blood circulation
- On irritated skin or area that is infected or reddened

Stop use and ask a doctor if discomfort lasts

Keep out of reach of children

If swallowed get medical help or contact a Poison Control Center immediately.

Directions:

Wash affected area, dry thoroughly
If necessary, cut medicated disk to fit corn
Apply medicated disk with sitcky side adhereing to skin
Cover medicated disk with enclosed cushion
After 48 hours, remove disk
Repeat procedure every 48 hours as needed for up to 14 days (until corn is removed)
May soak corn in warm water for 5 minutes to a

Other Information

Store between 15o C and 30o C (59o F and 86o F)

Inactive Ingredients

Vinyl Acetate